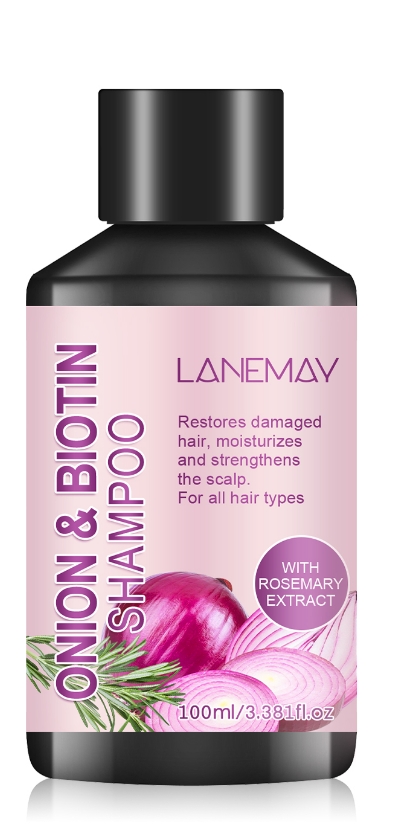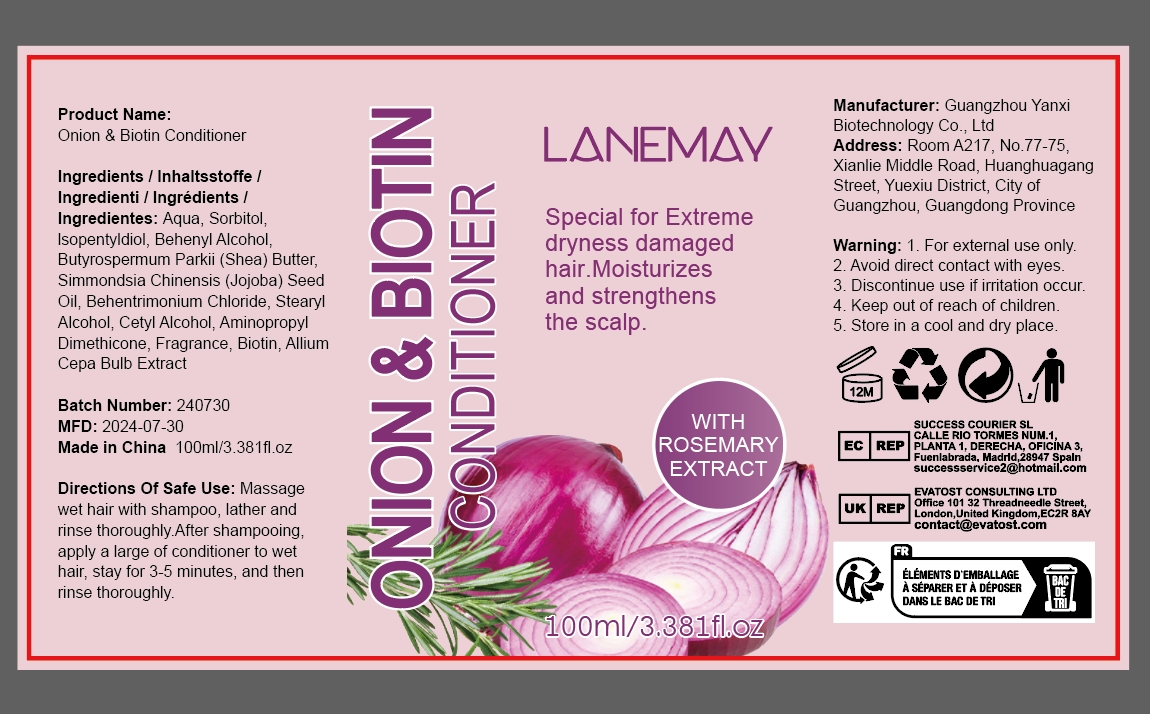 DRUG LABEL: Onion Biotin Conditioner
NDC: 84025-174 | Form: CREAM
Manufacturer: Guangzhou Yanxi Biotechnology Co.. Ltd
Category: otc | Type: HUMAN OTC DRUG LABEL
Date: 20240827

ACTIVE INGREDIENTS: DIPROPYLENE GLYCOL 3 mg/100 mL; SORBITOL 5 mg/100 mL
INACTIVE INGREDIENTS: WATER

DOSAGE AND ADMINISTRATION

Conditioner for relieving dry hair and smoothing hair

WARNINGS

keep out of children

INACTIVE INGREDIENT

AQUA

INDICATIONS AND USAGE

For daily hair care

keep out of children

PURPOSE

Effectively smoothes hair and keeps hair growing healthy